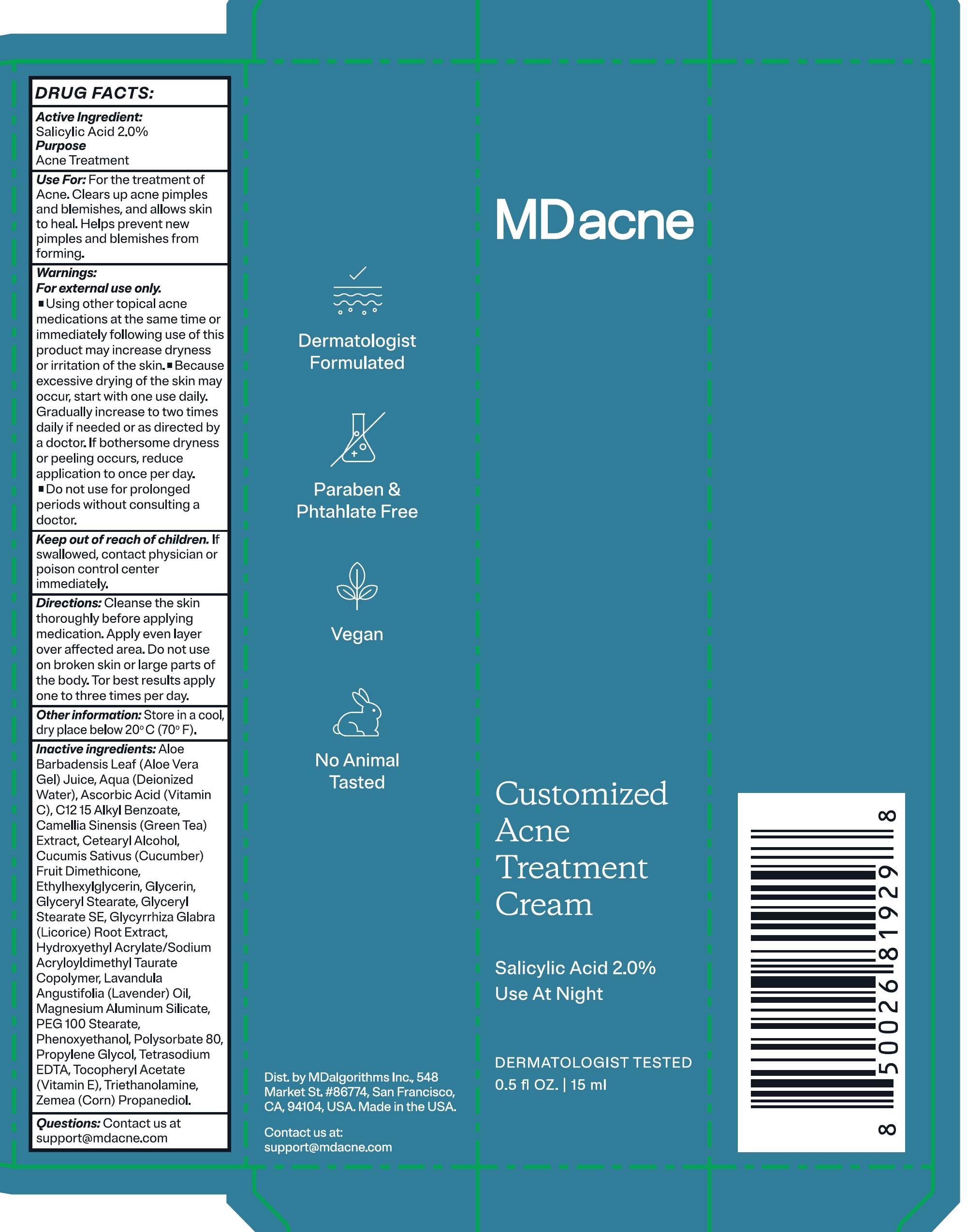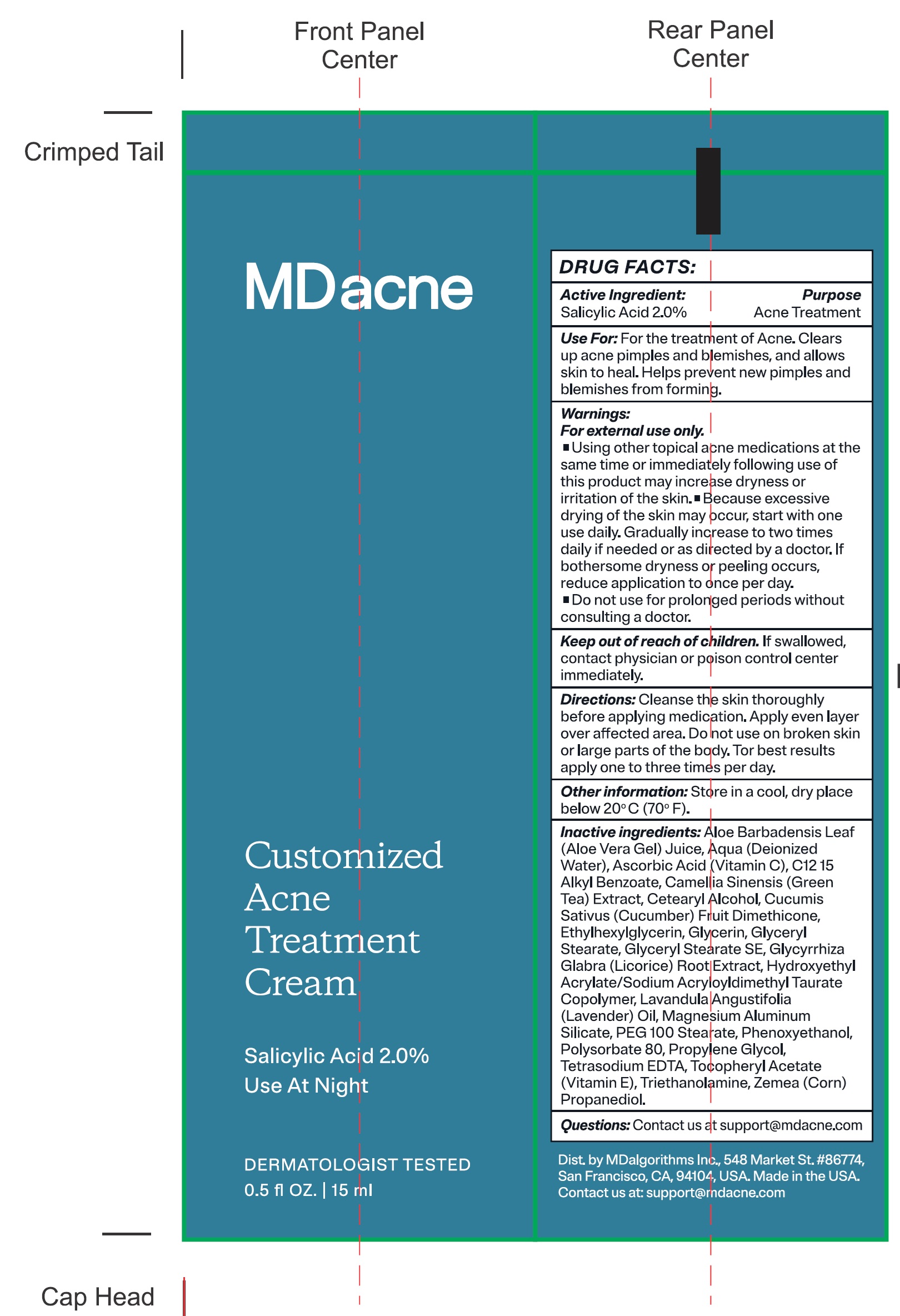 DRUG LABEL: MDacne Customized Acne Treatment Salicylic Acid
NDC: 71804-533 | Form: CREAM
Manufacturer: MDAlgorithms Inc
Category: otc | Type: HUMAN OTC DRUG LABEL
Date: 20240919

ACTIVE INGREDIENTS: SALICYLIC ACID 20 mg/1 mL
INACTIVE INGREDIENTS: ALOE VERA LEAF; WATER; ASCORBIC ACID; ALKYL (C12-15) BENZOATE; GREEN TEA LEAF; CETOSTEARYL ALCOHOL; CUCUMBER; DIMETHICONE, UNSPECIFIED; ETHYLHEXYLGLYCERIN; GLYCERIN; GLYCERYL MONOSTEARATE; GLYCERYL STEARATE SE; GLYCYRRHIZA GLABRA; LAVENDER OIL; MAGNESIUM ALUMINUM SILICATE; PEG-100 STEARATE; PHENOXYETHANOL; POLYSORBATE 80; PROPYLENE GLYCOL; EDETATE SODIUM; .ALPHA.-TOCOPHEROL ACETATE; CORN

MDacne Customized Acne Treatment Cream Salicylic Acid 2%

Active Ingredient:

Salicylic Acid 2.0%

Purpose

Acne Treatment

Use For:

For the treatment of Acne. Clears up acne pimples and blemishes, and allows skin to heal. Helps prevent new pimples and blemishes from forming.

Warnings:

For external use only.

- Using other topical acne medications at the same time or immediately following use of this product may increase dryness or irritation of the skin.
- Because excessive drying of the skin may occur, start with one use daily. Gradually increase to two times daily if needed or as directed by a doctor. If bothersome dryness or peeling occurs, reduce application to once per day.

• Do not use

for prolonged periods without consulting a doctor.

Keep out of reach of children.

If swallowed, contact physician or poison control center immediately.

Directions:

Cleanse the skin thoroughly before applying medication. Apply even layer over affected area. Do not use on broken skin or large parts of the body. *For best results apply one to three times per day.

Other information:

Store in a cool, dry place below 20ºC (70ºF).

Inactive Ingredients:

Aloe Barbadensis Leaf (Aloe Vera Gel) Juice, Aqua (Deionized Water), Ascorbic Acid (Vitamin C), C12 15 Alkyl Benzoate, Camellia Sinensis (Green Tea) Extract, Cetearyl Alcohol, Cucumis Sativus (Cucumber) Fruit Extract, Dimethicone, Ethylhexylglycerin, Glycerin, Glyceryl Stearate, Glyceryl Stearate SE, Glycyrrhiza Glabra (Licorice) Root Extract, Hydroxyethyl Acrylate/Sodium Acryloyldimethyl Taurate Copolymer, Lavandula Angustifolia (Lavender) Oil, Magnesium Aluminum Silicate, PEG 100 Stearate, Phenoxyethanol, Polysorbate 80, Propylene Glycol, Tetrasodium EDTA, Tocopheryl Acetate (Vitamin E), Zemea (Corn) Propanediol.

Questions:

Contact us at support@mdacne.com